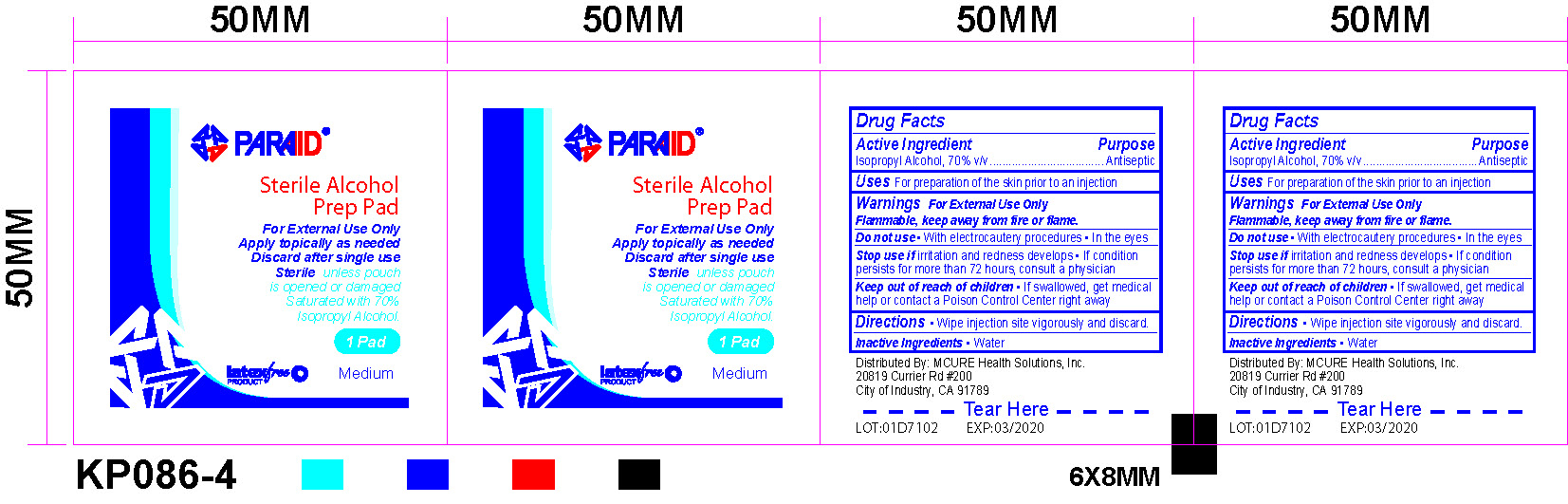 DRUG LABEL: Sterile Alcohol Prep Pad
NDC: 71310-001 | Form: SWAB
Manufacturer: Taizhou Kangping Medical Science And Technology Co., Ltd
Category: otc | Type: HUMAN OTC DRUG LABEL
Date: 20170815

ACTIVE INGREDIENTS: ISOPROPYL ALCOHOL 70 g/100 g
INACTIVE INGREDIENTS: WATER

Active Ingredient

Isopropyl Alcohol, 70% v/v

Purpose

Antiseptic

Uses

For preparation of the skin prior to an injection

Warnings

For External Use Only

Flammable, keep away from fire or flame.

Do not use

With electrocautery procedures
In the eyes

Stop use and ask a doctor

if irritation and redness develops
If condition persists for more than 72 hours, consult a physician

Keep out of reach of children

If swallowed, get medical help or contact a Poison Control Center right away

Directions

Wipe injection site vigorously and discard

Inactive Ingredients

Water